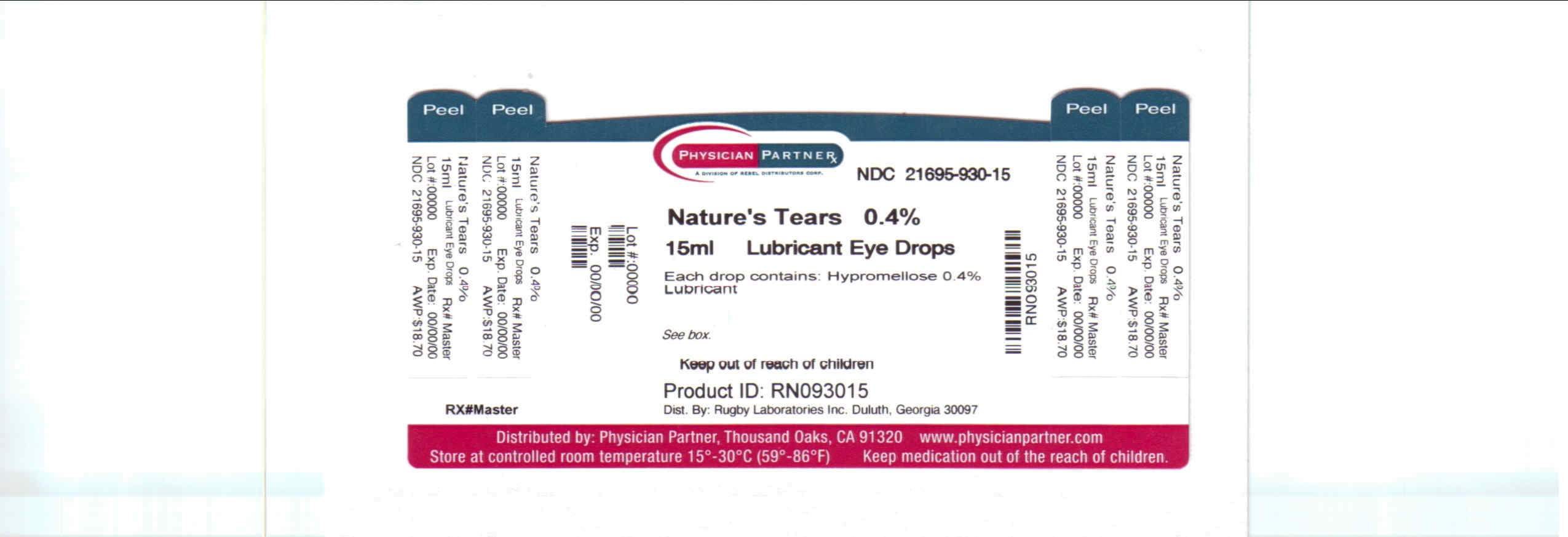 DRUG LABEL: Natures Tears
NDC: 21695-930 | Form: SOLUTION/ DROPS
Manufacturer: Rebel Distributors Corp
Category: otc | Type: HUMAN OTC DRUG LABEL
Date: 20110420

ACTIVE INGREDIENTS: HYPROMELLOSE 2910 (3 MPA.S) 4 mg/1 mL
INACTIVE INGREDIENTS: SODIUM PHOSPHATE, DIBASIC; EDETATE DISODIUM; SODIUM PHOSPHATE, MONOBASIC; POTASSIUM CHLORIDE; SODIUM CHLORIDE; WATER; BENZALKONIUM CHLORIDE

Nature's Tears Drug Facts

Active ingredient

Hypromellose

Purpose

Lubricant

Keep Out of Reach of Children

If swallowed, get medical help or contact a Poison Control Center right away.

Uses

° relieves dryness of the eye

° prevents further irritation

Warnings

Do not use if solution changes color or becomes cloudy

When using this product:

° do not touch tip of container to any surface to avoid contamination

° replace cap after use

Stop use and ask a doctor if:

° you experience eye pain, changes in vision, continued redness or irritation of the eye

° condition worsens or persists for more than 72 hours

Directions

° instill 1 or 2 drops in the affected eye(s) as needed

Other Information

° store at 15° - 30°C (59° - 85°F)

° keep tightly closed

FOR USE IN THE EYES ONLY

Inactive ingredients

dibasic sodium phosphate, edetate disodium, monobasic sodium phosphate,

potassium chloride, sodium chloride, purified water.

Hydrochloric acid and/or sodium hydroxide may be added to adjust pH.

Preservative added: benzalkonium chloride 0.01%

Questions of Comments?

Call 1-800-645-2158

9 am - 5 pm ET, Monday-Friday.

Serious side effects associated with use of this product may be reported to this number.

Distributed by:

Rugby Laboratories, Inc.

Duluth, GA 30097

Repackaged by:

Rebel Distributors Corp.

Thousand Oaks, CA 91320